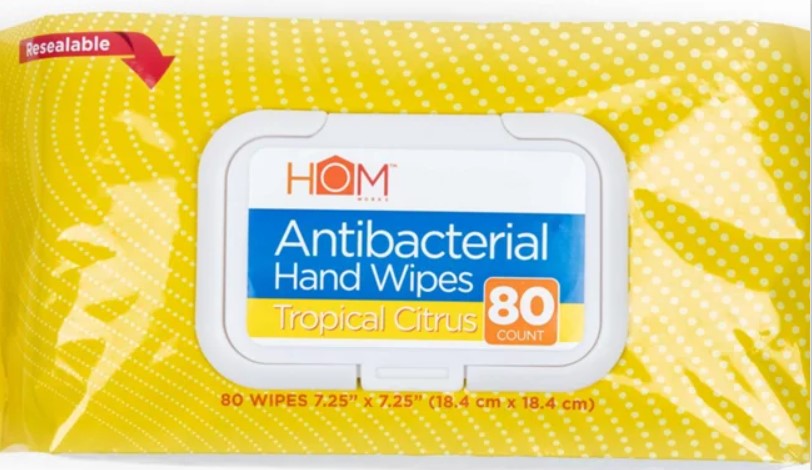 DRUG LABEL: Homworks Antibacterial Hand Wipes
NDC: 82131-325 | Form: SWAB
Manufacturer: Acadian Crossing Consumer Products, LLC.
Category: otc | Type: HUMAN OTC DRUG LABEL
Date: 20210726

ACTIVE INGREDIENTS: ALCOHOL 75 1/1 1
INACTIVE INGREDIENTS: GLYCERIN; WATER

Active Ingredient

Ethyl Alcohol 75% v/v

Purpose

Antiseptic

Use

Uses: • To help reduce bacteria that can potentially cause disease.

WARNINGS

Warnings: • For external use only; hands, general cleansing. • Does not replace wipes used for medical procedures. • Flammable; keep away from fire or flame. • Do not ingest.

When using this product: • Keep out of eyes. In case of contact with eyes, flush throughly with water. • Avoid contact with broken skin.

Stop use and ask a doctor if: • Irritation and redness develop. • Condition persists for more than 72 hours.

Keep out of reach of children: • If swallowed, get medical help or contact a poison control center right away.

Directions

Directions: • Single use wipes for hands. • Close properly after dispensing to maintain purity, as alcohol by its nature evaporates quickly. • Dispose of properly. • DO NOT FLUSH. • Apply throughly to hands to cover all surfaces. • Rub hand together until dry.

Other Information

Keep out of light; store at room temperature 59ºF-86ºF.

INACTIVE INGREDIENT

Fragrance, Gylcerol, Water.